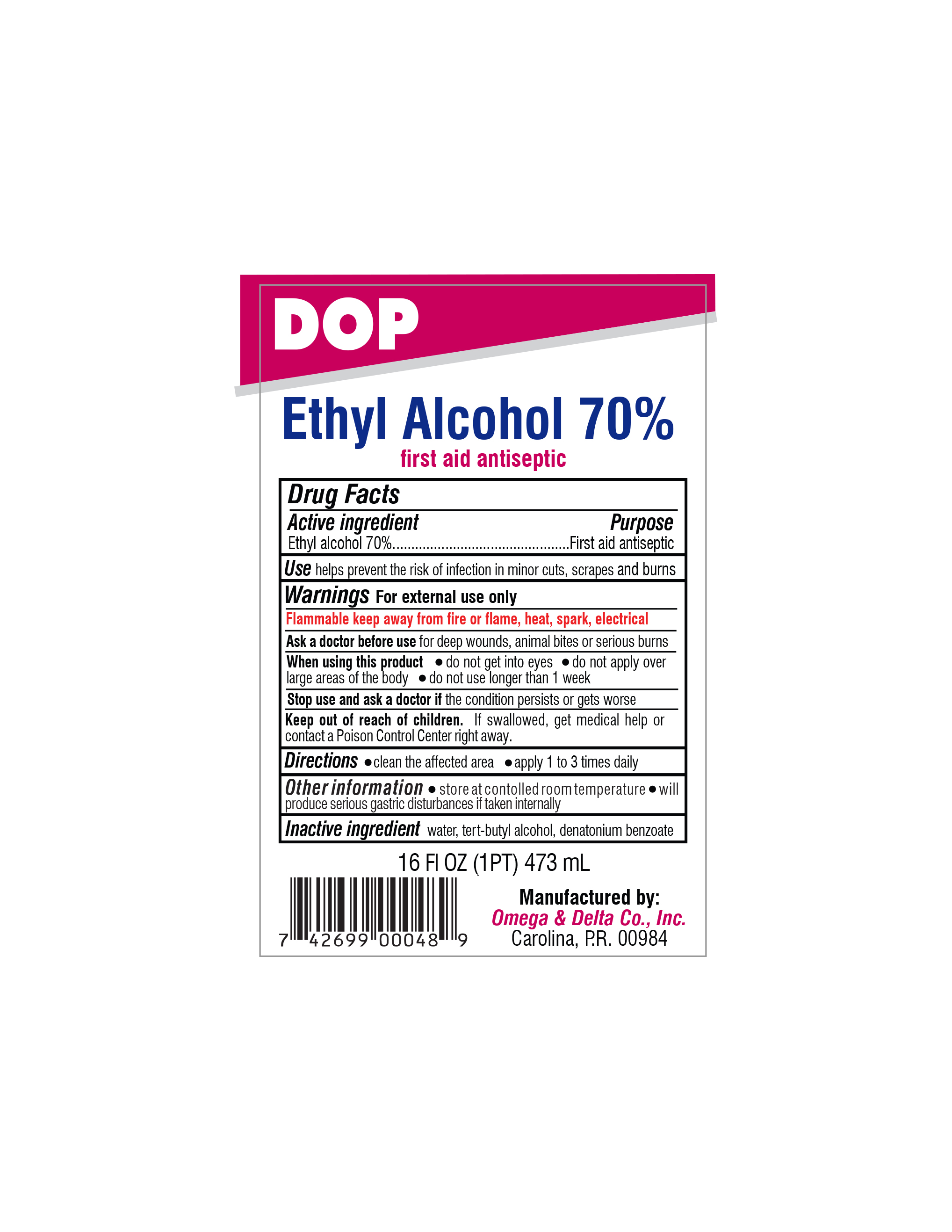 DRUG LABEL: DOP Ethyl Alcohol 70%
NDC: 51048-048 | Form: LIQUID
Manufacturer: Omega & Delta Co., Inc.
Category: otc | Type: HUMAN OTC DRUG LABEL
Date: 20260121

ACTIVE INGREDIENTS: ALCOHOL 70 mL/100 mL
INACTIVE INGREDIENTS: WATER

DOP Ethyl Alcohol 70%

Active ingredient

Ethyl alcohol 70%

Purpose

First aid antiseptic

Keep out of reach of children. If swallowed, get medical help or contact a Poison Control Center right away.

INDICATIONS AND USAGE

Use helps prevent the risk of infection in minor cuts, scrapes and burns

Warnings For external use only

Flammable keep away from fire or flame, heat, spark, electrical

Ask a doctor before use for deep wounds, animal bites or serious burns

When using this product • do not get into eyes • do not apply over large area of the body • do not use longer than 1 week

Stop use and ask a doctor if the condition persists or gets worse

DOSAGE AND ADMINISTRATION

Directions • clean the affected area • apply 1 to 3 times daily

Inactive ingredient Purified water

Other information • store at controlled temperature • will produce serious gastric disturbances if taken internally

Manufactured by:

Omega & Delta Co., Inc.

Carolina, P.R. 00984